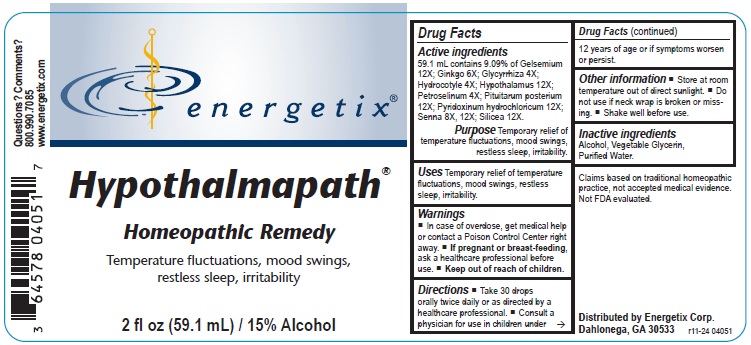 DRUG LABEL: Hypothalmapath
NDC: 64578-0171 | Form: LIQUID
Manufacturer: Energetix Corporation
Category: homeopathic | Type: HUMAN OTC DRUG LABEL
Date: 20241120

ACTIVE INGREDIENTS: GELSEMIUM SEMPERVIRENS ROOT 12 [hp_X]/59.1 mL; GINKGO 6 [hp_X]/59.1 mL; LICORICE 4 [hp_X]/59.1 mL; CENTELLA ASIATICA WHOLE 4 [hp_X]/59.1 mL; BOS TAURUS HYPOTHALAMUS 12 [hp_X]/59.1 mL; PETROSELINUM CRISPUM WHOLE 4 [hp_X]/59.1 mL; SUS SCROFA PITUITARY GLAND, POSTERIOR 12 [hp_X]/59.1 mL; PYRIDOXINE HYDROCHLORIDE 12 [hp_X]/59.1 mL; SENNA LEAF 8 [hp_X]/59.1 mL; SILICON DIOXIDE 12 [hp_X]/59.1 mL
INACTIVE INGREDIENTS: ALCOHOL; GLYCERIN; WATER

Hypothalmapath

ACTIVE INGREDIENT

Active ingredients59.1 mL contains 9.09% of Gelsemium 12X; Ginkgo 6X; Glycyrrhiza 4X; Hydrocotyle 4X; Hypothalamus 12X; Petroselinum 4X; Pituitarum posterium 12X; Pyridoxinum hydrochloricum 12X; Senna 8X, 12X; Silicea 12X.

Claims based on traditional homeopathic practice, not accepted medical evidence. Not FDA evaluated.

Uses

Temporary relief of temperature fluctuations, mood swings, restless sleep, irritability.

Warnings

- In case of overdose, get medical help or contact a Poison Control Center right away.
- If pregnant or breast-feeding, ask a healthcare professional before use.

- Keep out of reach of children.

Directions

- Take 30 drops orally twice daily or as directed by a healthcare professional.
- Consult a physician for use in children under 12 years of age or if symptoms worsen or persist.

Other information

- Store at room temperature out of direct sunlight.
- Do not use if neck wrap is broken or missing.
- Shake well before use.

Inactive ingredients

Alcohol, Vegetable Glycerin, Purified Water.

QUESTIONS

Distributed by Energetix Corp.

Dahlonega, GA 30533

Questions? Comments?

800.990.7085

www.energetix.com

PACKAGE LABEL

energetix

Hypothalmapath

Homeopathic Remedy

Temperature fluctuations, mood swings, restless sleep, irritability

2 fl oz (59.1 mL) / 15% Alcohol

Purpose

Temporary relief of temperature fluctuations, mood swings, restless sleep, irritability.